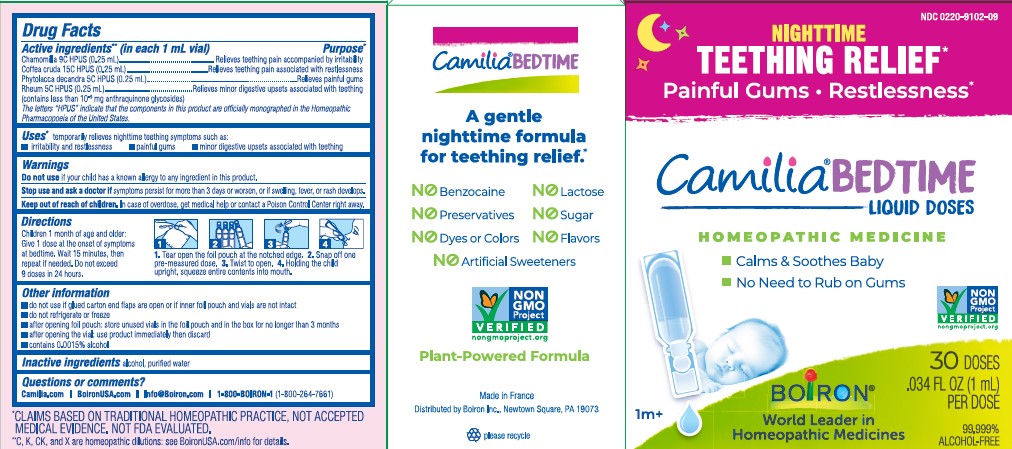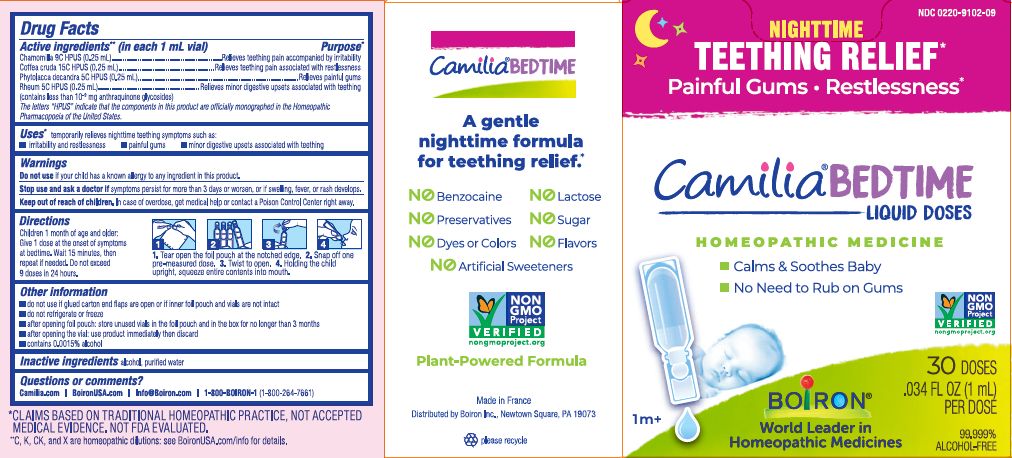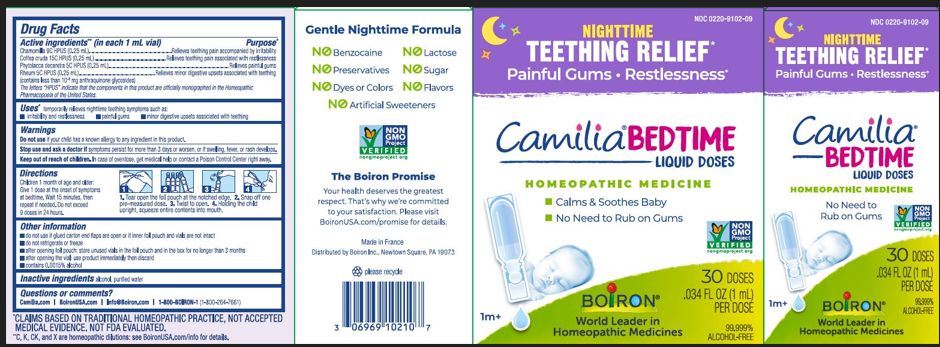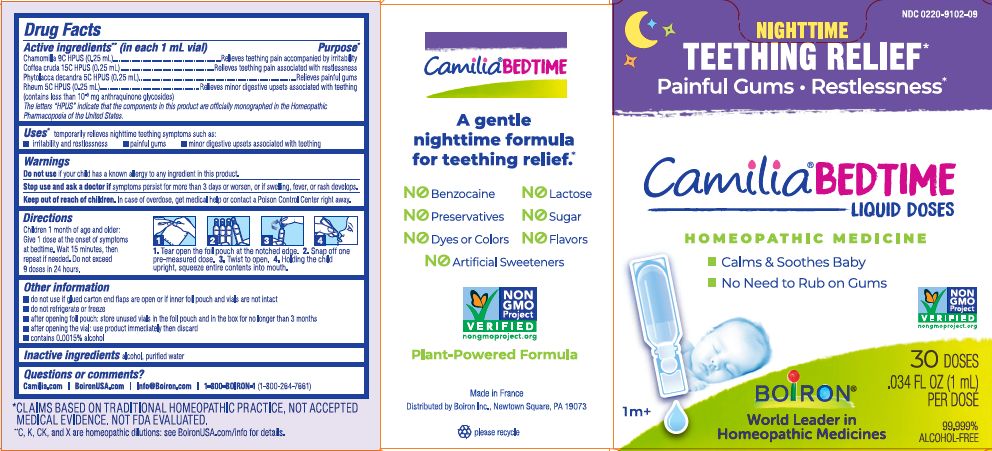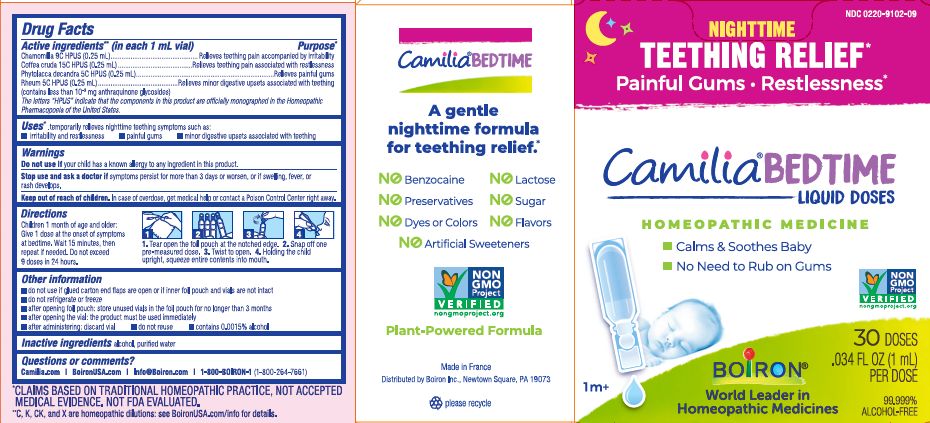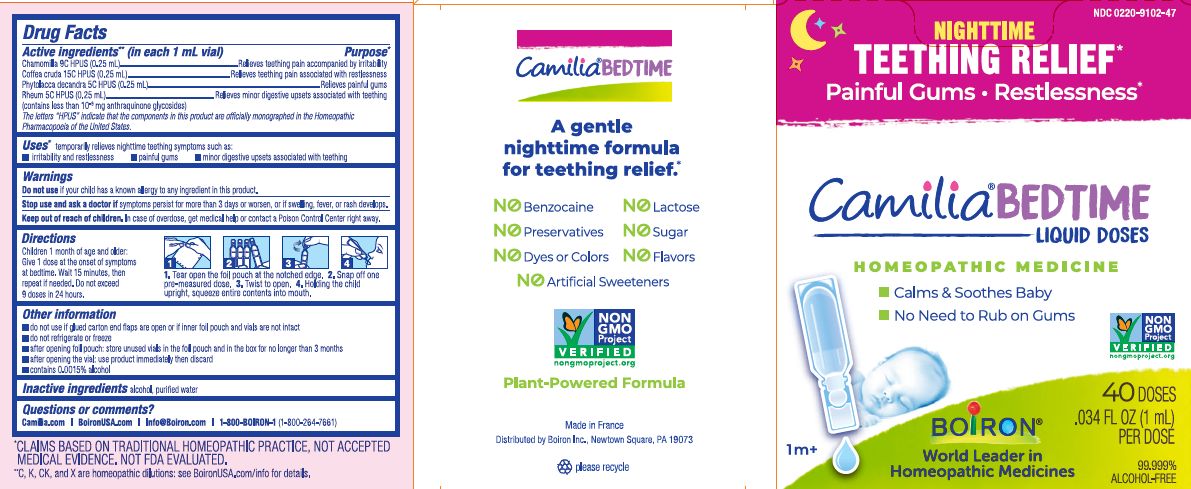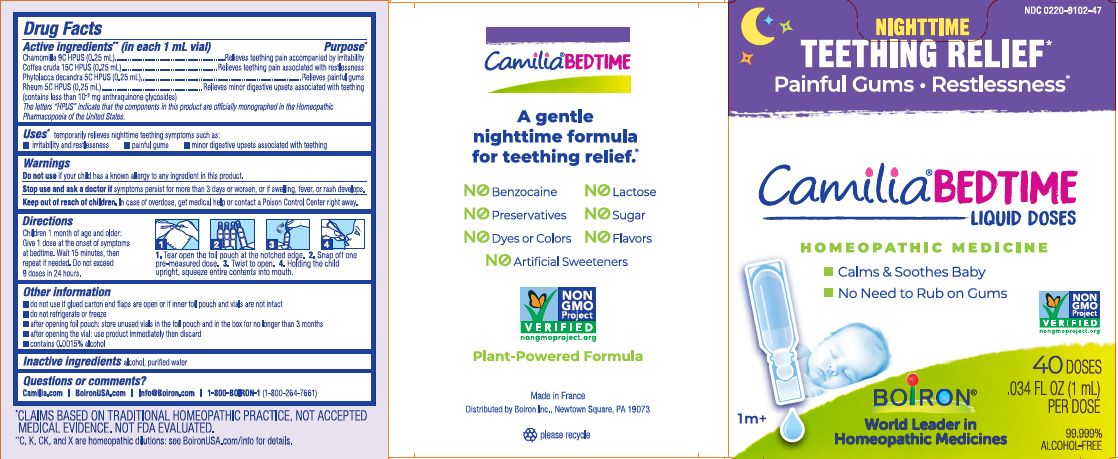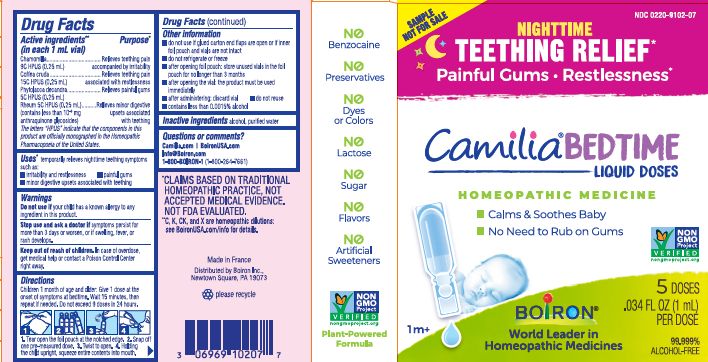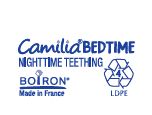 DRUG LABEL: Camilia Bedtime
NDC: 0220-9102 | Form: LIQUID
Manufacturer: Boiron
Category: homeopathic | Type: HUMAN OTC DRUG LABEL
Date: 20260113

ACTIVE INGREDIENTS: PHYTOLACCA AMERICANA ROOT 5 [hp_C]/1 1; MATRICARIA CHAMOMILLA 9 [hp_C]/1 1; RHEUM OFFICINALE ROOT 5 [hp_C]/1 1; ARABICA COFFEE BEAN 15 [hp_C]/1 1
INACTIVE INGREDIENTS: ALCOHOL; WATER

Camilia Bedtime

Active ingredients** (in each 1 mL vial)

Chamomilla 9C HPUS (0.25 mL)

Coffea cruda 15C HPUS (0.25 mL)

Phytolacca decandra 5C HPUS (0.25 mL)

Rheum 5C HPUS (0.25 mL) (contains less than 10^-9 mg anthraquinone glycosides)

The letters "HPUS" indicate that the components in this product are officially monographed in the Homeopathic Pharmacopoeia of the United States.

Purpose*

Chamomilla 9C HPUS (0.25 mL) ... Relieves teething pain accompanied by irritability

Coffea cruda 15C HPUS (0.25 mL) ... Relieves teething pain associated with restlessness

Phytolacca decandra 5C HPUS (0.25 mL) ... Relieves painful gums

Rheum 5C HPUS (0.25 mL) ... Relieves minor digestive upsets associated with teething

INDICATIONS AND USAGE

temporarily relieves nighttime teething symptoms such as:

- irritability and restlessness
- painful gums
- minor digestive upsets associated with teething

Do not use if your child has a known allergy to any ingredient in this product.

Stop use and ask a doctor if symptoms persist for more than 3 days or worsen, or if swelling, fever, or rash develops.

Keep out of reach of children. In case of overdose, get medical help or contact a Poison Control Center right away.

DOSAGE AND ADMINISTRATION

Children 1 month of age and older: Give 1 dose at the onset of symptoms at bedtime. Wait 15 minutes, then repeat if needed. Do not exceed 9 doses in 24 hours.

1. Tear open foil pouch at the notched edge. 2. Snap off one pre-measured dose. 3. Twist to open. 4. Holding the child upright, squeeze entire contents in the mouth.

INACTIVE INGREDIENT

alcohol, purified water

QUESTIONS

Camilia.com

Boiron USA.com

Info@Boiron.com

1-800-BOIRON-1

(1-800-264-7661)

- do not use if glued carton end flaps are open if inner foil pouch and vials are not intact
- do not refrigerate or freeze
- after opening foil pouch: store unused vials in the foil pouch and in the box for no longer than 3 months
- after opening the vial: use product immediately then discard
- contains 0.0015% alcohol

5 DOSES .034 FL OZ (1 mL) PER DOSE

30 DOSES .034 FL OZ (1 mL) PER DOSE

40 DOSES .034 FL OZ (1 mL) PER DOSE

99.999% ALCOHOL-FREE

Nighttime Teething Relief*

Painful Gums Restlessness*

*CLAIMS BASED ON TRADITIONAL HOMEOPATHIC PRACTICE, NOT ACCEPTED MEDICAL EVIDENCE. NOT FDA EVALUATED.
**C,K,CK, and X are homeopathic dilutions: see BoironUSA.com/info for details.